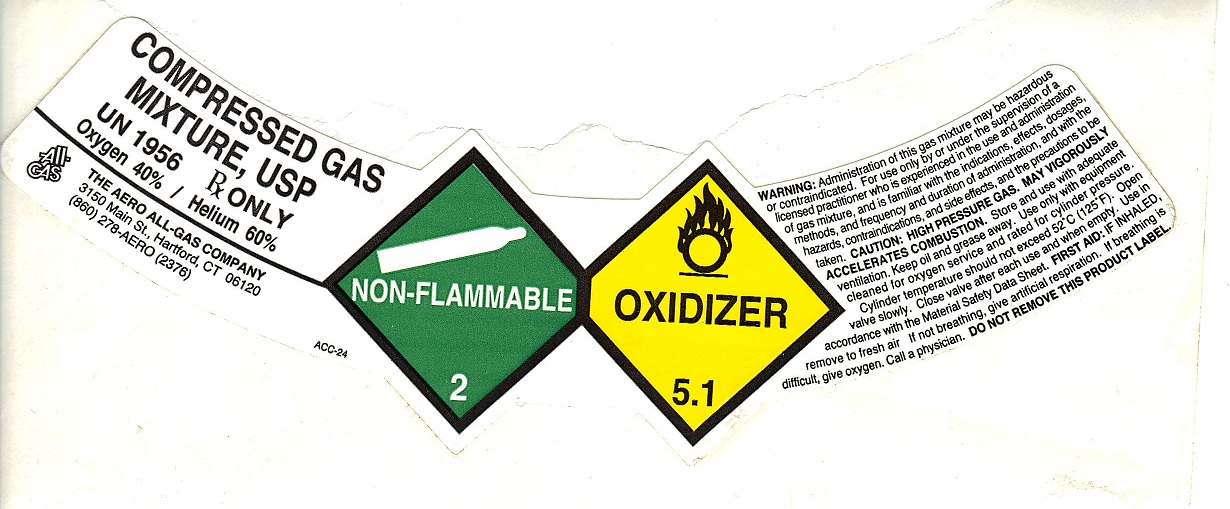 DRUG LABEL: Oxygen Helium Mixture 40/60
NDC: 10014-007 | Form: GAS
Manufacturer: Aero All Gas Company
Category: prescription | Type: HUMAN PRESCRIPTION DRUG LABEL
Date: 20100525

ACTIVE INGREDIENTS: Oxygen 400 mL/1 L; Helium 600 mL/1 L

O2 40 HE 60 MIX

PACKAGE LABEL

COMPRESSED GAS MIXTURE, USP UN1956 Rx ONLY
Oxygen 40%/ Helium 60%
ALL-GAS THE AERO ALL-GAS COMPANY 3150 Main St. Hartford, CT 06120 (860) 278-AERO (2376)
ACC-24
NON-FLAMMABLE GAS 2 OXIDIZER 5.1
WARNING: Administration of this gas mixture may be hazardous or contraindicated. For use only by or under the supervision of a licensed practitioner who is experienced in the use administration of gas mixture, and is familiar with the indications, effects, dosages, methods, and frequency and duration of administration, and with the hazards, contraindications and side effects and the precautions to be taken. CAUTION: HIGH PRESSURE GAS. MAY VIGOROUSLY ACCELERATE COMBUSTION. Store and use with adequate ventilation. Keep oil and grease away. Use only with equipment cleaned for oxygen service and rated for cylinder pressure. Cylinder temperature should not exceed 52C (125F). Open valve slowly. Close valve after each use and when empty. Use in accordance with the Material Safety Data Sheet. FIRST AID: IF INHALED, remove to fresh air. If not breathing, give artificial respiration. If breathing is difficult, give oxygen. Call a physician. DO NOT REMOVE THIS PRODUCT LABEL.